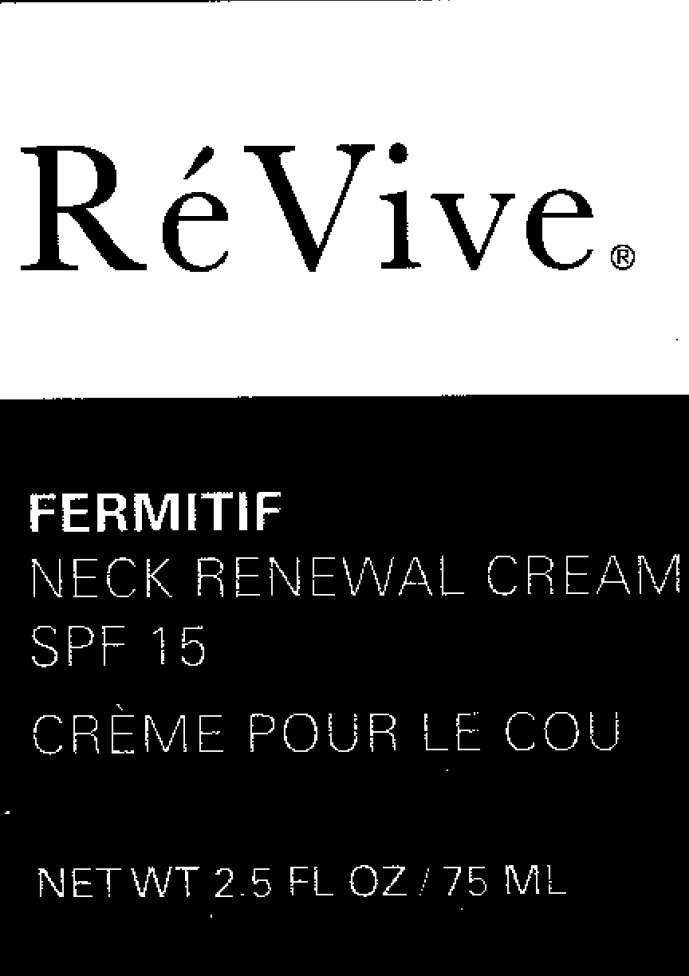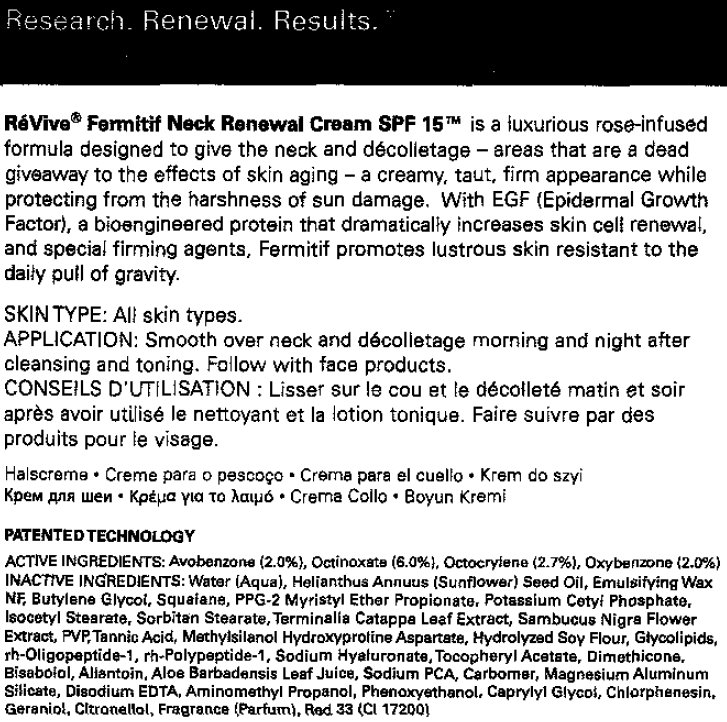 DRUG LABEL: ReVive Fermitif Neck Renewal SPF 15
NDC: 65342-1230 | Form: CREAM
Manufacturer: Gurwitch Products, LLC
Category: otc | Type: HUMAN OTC DRUG LABEL
Date: 20231212

ACTIVE INGREDIENTS: AVOBENZONE 20 mg/1 mL; OCTINOXATE 60 mg/1 mL; OCTOCRYLENE 27 mg/1 mL; OXYBENZONE 20 mg/1 mL
INACTIVE INGREDIENTS: WATER; SUNFLOWER OIL; BUTYLENE GLYCOL; POTASSIUM CETYL PHOSPHATE; SORBITAN MONOSTEARATE; SAMBUCUS NIGRA FLOWER; TANNIC ACID; HYALURONATE SODIUM; DIMETHICONE; LEVOMENOL; ALOE VERA LEAF; SODIUM PYRROLIDONE CARBOXYLATE; MAGNESIUM ALUMINUM SILICATE; EDETATE DISODIUM; AMINOMETHYLPROPANOL; PHENOXYETHANOL; CAPRYLYL GLYCOL; CHLORPHENESIN; GERANIOL; D&C RED NO. 33

ReVive Fermitif Neck Renewal Cream SPF 15

ACTIVE INGREDIENT

ACTIVE INGREDIENTS: Avobenzone (2.0%), Octinoxate (6.0%), Octocrylene (2.7%), Oxybenzone (2.0%).

INACTIVE INGREDIENT

INACTIVE INGREDIENTS: Water (Aqua), Helianthus Annuus (Sunflower) Seed Oil, Emulsifying Wax NF, Butylene Glycol, Squaiane, PPG-2 Myristyl Ether Propionate, Potassium Cetyl Phosphate, Isocetyl Stearate, Sorbitan Stearate, Terminalia Catappa Leaf Extract, Sambucus Nigra Flower Extract, PVP, Tannic Acid, Methylsilanol Hydroxyproline Aspartate, Hydrolyzed Soy Flour, Glycolipids, rh-Oligopeptide-1, rh-Polypeptide-1, Sodium Hyaluronate, Tocopheryl Acetate, Dimethicone, Bisabolol, Aliantoin, Aloe Barbadensis Leaf Juice, Sodium PCA, Carbomer, Magnesium Aluminum Silicate, Disodium EDTA, Aminomethyl Propanol, Phenoxyethanol, Caprylyl Glycol, Chlorphenesin, Geraniol, Citronellol, Fragrance (Parfum), Red 33 (CI 17200).

WHEN USING

APPLICATION: Smooth over neck and decolletage morning and night after cleansing and toing. Follow with face products.

PURPOSE

SKIN TYPE: All skin types.

DESCRIPTION

ReVive Fermitif Neck Renewal Cream SPF 15 is a luxurious rose-infused formula designed to give the neck and decolletage - areas that are a dead giveaway to the effects of skin aging - a creamy, taut, firm appearance while protecting from the harshness of sun damage. With EGF (Epidermal Growth Factor), a bioengineered protein that dramatically increases skin cell renewal, and special firming agents. Fermitif promotes lustrous skin resistant to the daily pull of gravity.

PACKAGE LABEL

Re Vive FERMITIF NECK RENEWAL CREAM SPF 15 CREME POUR LE COU NET WT 2.5 FL OZ / 75 ML

PACKAGE LABEL

Research Renewal Results. ReVive Fermitif Neck Renewal Cream SPF 15 PATENTED TECHNOLOGY.